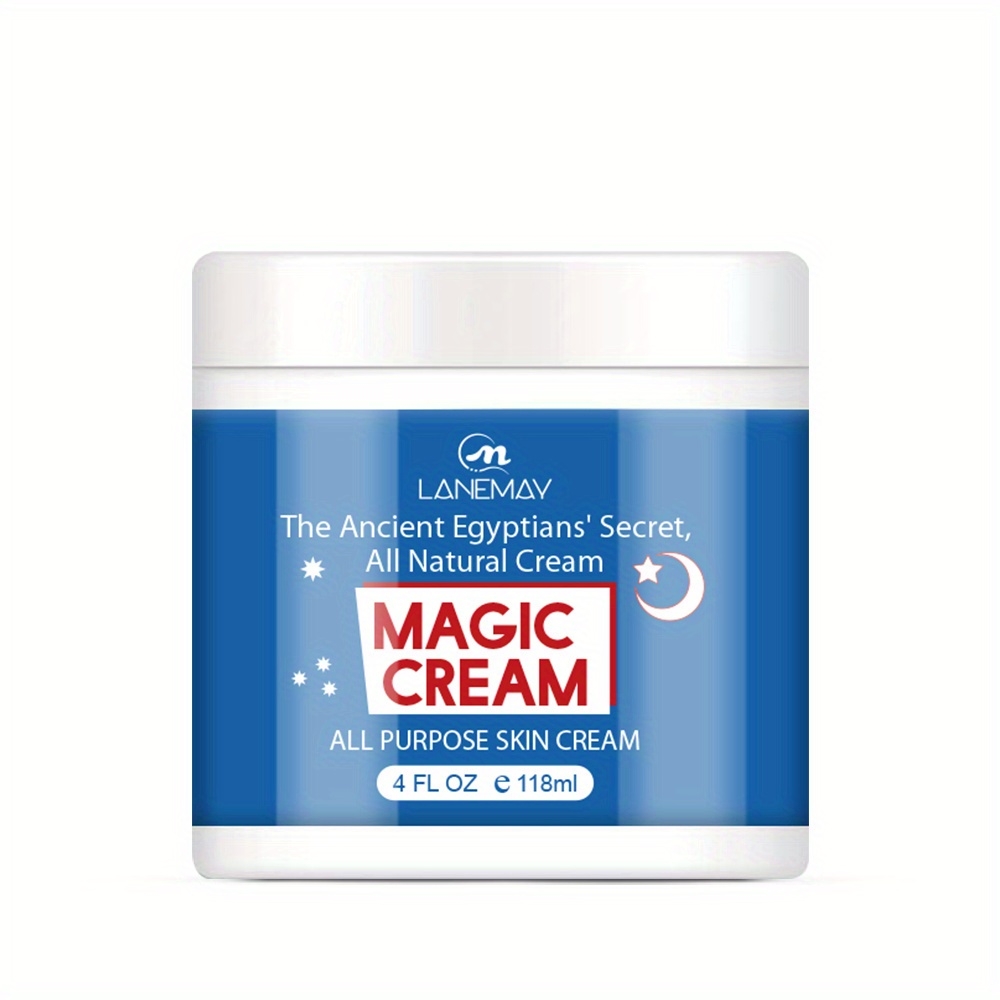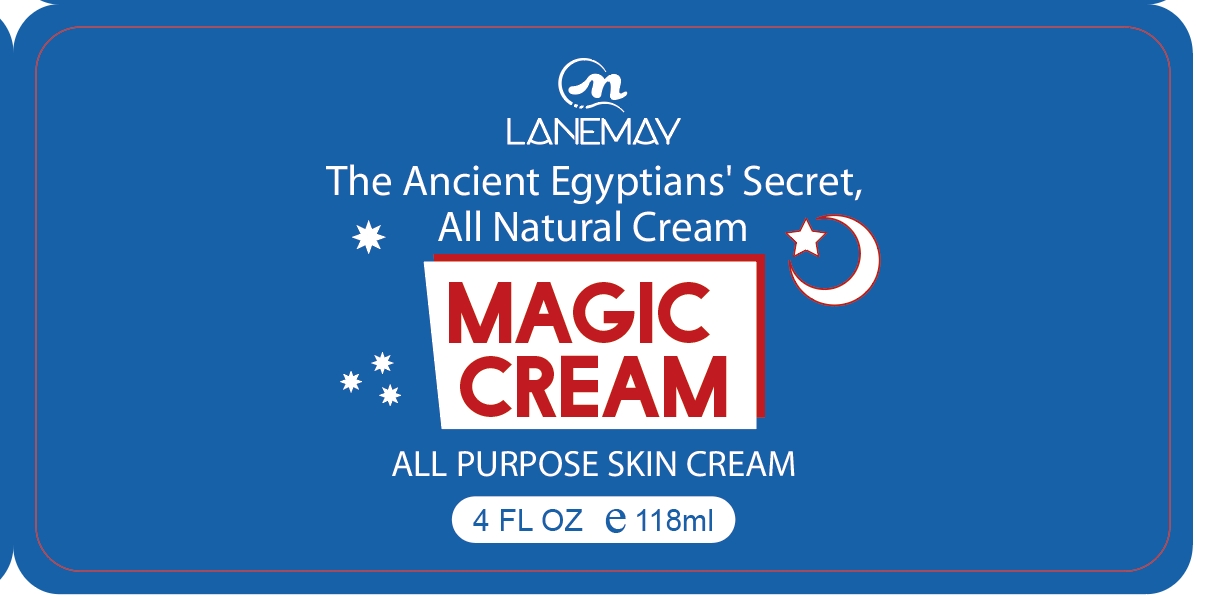 DRUG LABEL: Magic Cream
NDC: 84025-029 | Form: CREAM
Manufacturer: Guangzhou Yanxi Biotechnology Co., Ltd
Category: otc | Type: HUMAN OTC DRUG LABEL
Date: 20240403

ACTIVE INGREDIENTS: SQUALANE 5 mg/50 mL; GLYCERIN 5 mg/50 mL
INACTIVE INGREDIENTS: WATER

INACTIVE INGREDIENT

Aqua

DOSAGE AND ADMINISTRATION

use as a normal facial cream

WARNINGS

For external use only.

INDICATIONS AND USAGE

Apply to affected area twice per day on cleansed skin.

Keep out of reach of children.

PURPOSE

soften and smooth skin